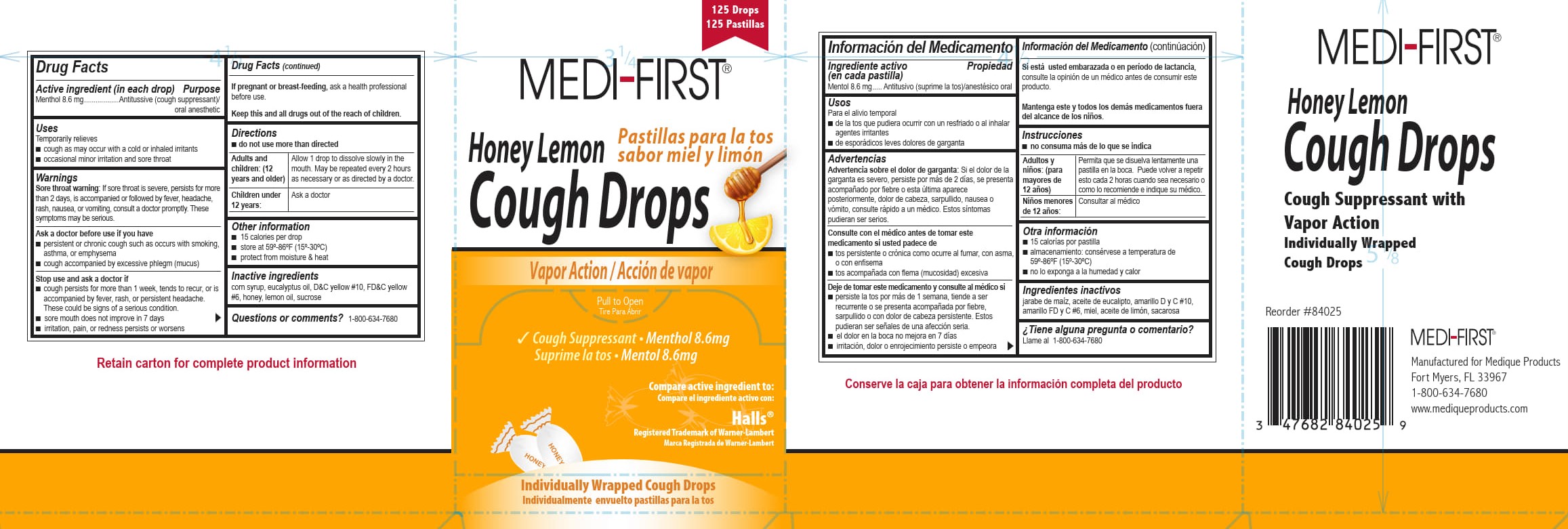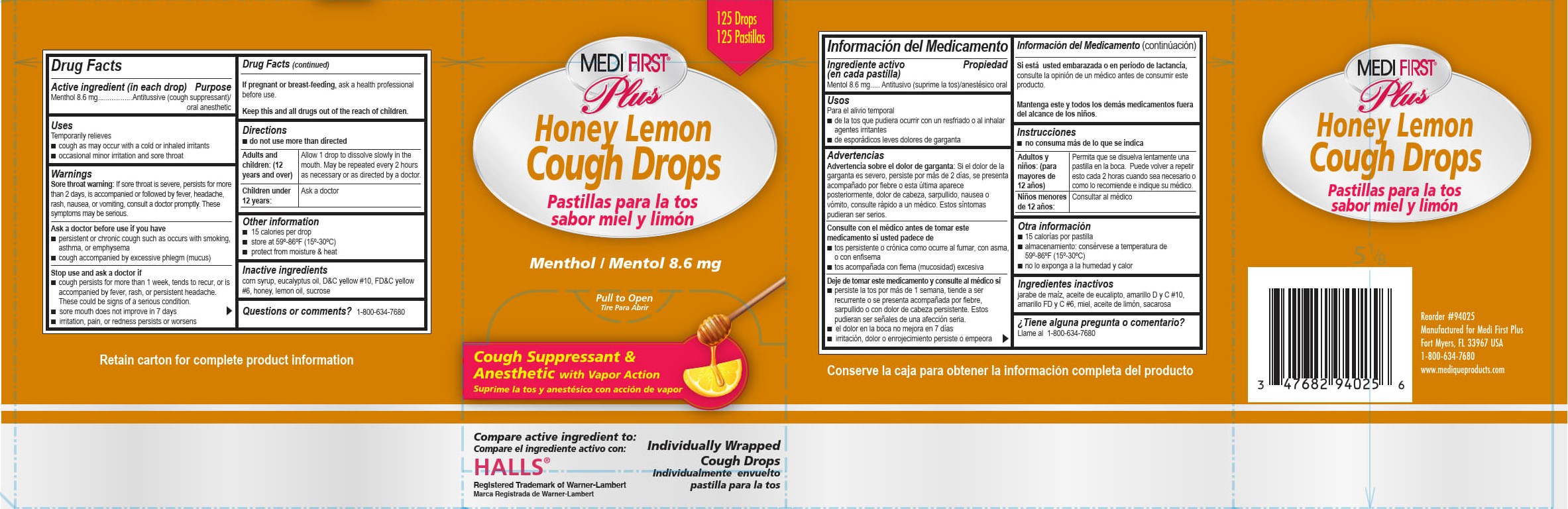 DRUG LABEL: Medi-First Honey Lemon Cough Drops
NDC: 47682-840 | Form: LOZENGE
Manufacturer: Unifirst First Aid Corporation
Category: otc | Type: HUMAN OTC DRUG LABEL
Date: 20250909

ACTIVE INGREDIENTS: MENTHOL 8.6 mg/1 1
INACTIVE INGREDIENTS: CORN SYRUP; D&C YELLOW NO. 10; FD&C YELLOW NO. 6; EUCALYPTUS OIL; HONEY; LEMON OIL; SUCROSE

Medi-First Honey Lemon Cough Drop

Drug Facts

Active ingredient (in each drop)

Menthol 8.6 mg

Purpose

Antitussive (cough suppressant)/oral anesthetic

Uses

Temporarily relieves

■ cough as may occur with a cold or inhaled irritants

■ occasional minor irritation and sore throat

Warnings

Sore throat warning: If sore throat is severe, persists for more than 2 days, is accompanied or followed by fever, headache, rash, nausea, or vomiting, consult a doctor promptly. These symptoms may be serious.

Ask a doctor before use if you have

■ persistent or chronic cough such as occurs with smoking, asthma, or emphysema

■ cough accompanied by excessive phlegm (mucus)

Stop use and ask a doctor if

■ cough persists for more than 7 days, tends to recur, or is accompanied by fever, rash, or persistent

headache. These could be signs of a serious condition.

■ sore mouth does not improve in 7 days

■ irritation, pain, or redness persists or worsens

PREGNANCY OR BREAST FEEDING

If pregnant or breast-feeding, ask a health professional before use.

KEEP OUT OF REACH OF CHILDREN

Keep this and all drugs out of the reach of children.

Directions

■ do not use more than directed

Adults and children: (12 years and older)

Allow 1 drop to dissolve slowly in the mouth. May be repeated every 2 hours as necessary or as directed by a doctor.

Children under 12 years:

Ask a doctor

Other information

■ 15 calories per drop

■ store at 59º-86ºF (15º-30ºC)

■ protect from moisture & heat

Inactive ingredients

corn syrup, eucalyptus oil, D&C yellow #10, FD&C yellow #6, honey, lemon oil, sucrose

Questions or comments? 1-800-634-7680

PACKAGE LABEL

Medi-First Plus ®

Honey Lemon

Cough Drops

125 Drops

125 Pastillas

Pastillas para la tos

sabor miel y limon

Menthol / Mentol 8.6 mg

Pull to Open

Tire Para Abrir

Cough Suppressant &

Anesthetic with Vapor Action

Suprime la tos y anestésico con acción de vapor

Compare active ingredients to:

Compare el ingredient active con:

Halls®

Registered Trademark of Warner-Lambert

Marca Registrada de Warner-Lambert

Individually Wrapped Cough Drops

Individualmente envuelto pastillas para la tos

PACKAGE LABEL

125 Drops

125 Pastillas

Medi First®

Honey Lemon

Cough Drops

Pastillas para la tos

sabor miel y limon

Vapor Action / Accion de vapor

Pull to Open

Tire Para Abrir

Cough Suppressant • Menthol 8.6 mg

Suprime la tos • Mentol 8.6 mg

Compare active ingredients to:

Compare el ingredient active con:

Halls®

Registered Trademark of Warner-Lambert

Marca Registrada de Warner-Lambert

Individually Wrapped Cough Drops

Individualmente envuelto pastillas para la tos